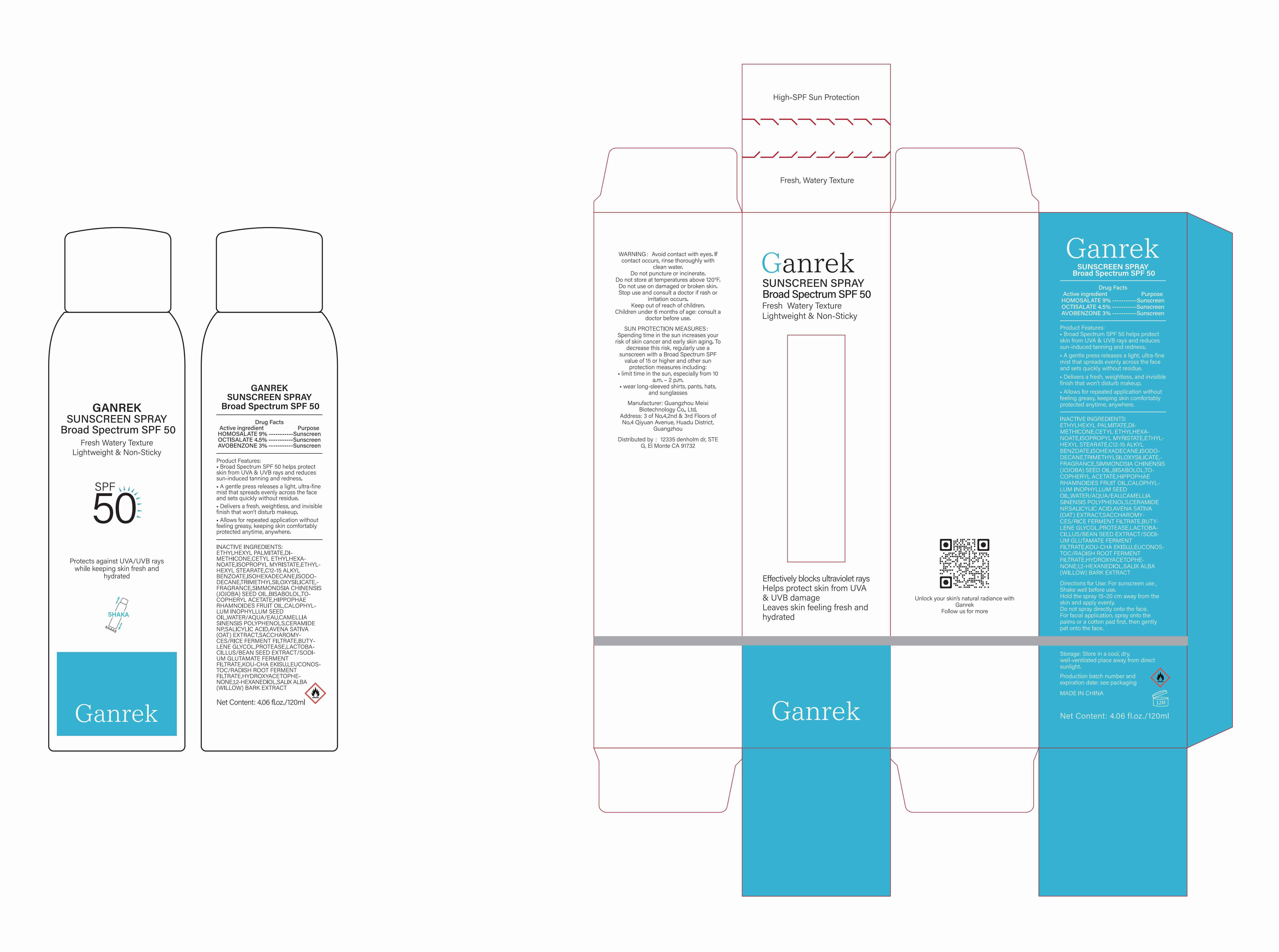 DRUG LABEL: Ganrek SUNSCREEN SPRAYER Broad Spectrum SPF 50
NDC: 84167-424 | Form: AEROSOL, SPRAY
Manufacturer: Guangzhou Meixi Biotechnology Co., Ltd.
Category: otc | Type: HUMAN OTC DRUG LABEL
Date: 20260210

ACTIVE INGREDIENTS: HOMOSALATE 1 g/1 1; OCTISALATE 1 g/1 1; AVOBENZONE 1 g/1 1
INACTIVE INGREDIENTS: BISABOLOL; ISOPROPYL MYRISTATE; HYDROXYACETOPHENONE; CETYL ETHYLHEXANOATE; C12-15 ALKYL BENZOATE; LEUCONOSTOC/RADISH ROOT FERMENT FILTRATE; ETHYLHEXYL PALMITATE; CAMELLIA SINENSIS SEED; TRIMETHYLSILOXYSILICATE (M/Q 0.6-0.8); SALIX ALBA BARK; SACCHAROMYCES CEREVISIAE; ETHYLHEXYL STEARATE; BUTYLENE GLYCOL; .ALPHA.-TOCOPHEROL ACETATE; WATER; HIPPOPHAE RHAMNOIDES FRUIT OIL; ISODODECANE; AVENA SATIVA (OAT) BRAN; ISOHEXADECANE; CAMELLIA SINENSIS WHOLE; FRAGRANCE 13576; SIMMONDSIA CHINENSIS (JOJOBA) SEED OIL; CALOPHYLLUM INOPHYLLUM SEED OIL; MUNG BEAN; DIMETHICONE; LIPROTAMASE PROTEASE; 1,2-HEXANEDIOL; SALICYLIC ACID; CERAMIDE NP

ACTIVE INGREDIENT

HOMOSALATE ；
OCTISALATE ；
AVOBENZONE 。

INACTIVE INGREDIENT

INACTIVE INGREDIENTS:ETHYLHEXYL PALMITATE,DIMETHICONE,CETYL ETHYLHEXANOATE,ISOPROPYL MYRISTATE,ETHYLHEXYL STEARATE,C12-15 ALKYL BENZOATE,ISOHEXADECANE,ISODODECANE,TRIMETHYLSILOXYSILICATE,FRAGRANCE,SIMMONDSIA CHINENSIS (JOJOBA) SEED OIL,BISABOLOL,TOCOPHERYL ACETATE,HIPPOPHAE RHAMNOIDES FRUIT OIL,CALOPHYLLUM INOPHYLLUM SEED OIL,WATER/AQUA/EAU,CAMELLIA SINENSIS POLYPHENOLS,CERAMIDE NP,SALICYLIC ACID,AVENA SATIVA (OAT) EXTRACT,SACCHAROMYCES/RICE FERMENT FILTRATE,BUTYLENE GLYCOL,PROTEASE,LACTOBACILLUS/BEAN SEED EXTRACT/SODIUM GLUTAMATE FERMENT FILTRATE,KOU-CHA EKISU,LEUCONOSTOC/RADISH ROOT FERMENT FILTRATE,HYDROXYACETOPHENONE,1,2-HEXANEDIOL,SALIX ALBA (WILLOW) BARK EXTRACT

DOSAGE AND ADMINISTRATION

Net Content: 4.06 fl.oz./120ml

KEEP OUT OF REACH OF CHILDREN

Do not spray directly onto the face.For facial application, spray onto thepalms or a cotton pad first, then gentlypat onto the face.

keep out of reach of children

INDICATIONS AND USAGE

Directions for Use: For sunscreen useShake well before use.Hold the spray 15-20 cm away from theskin and apply evenly.Do not spray directly onto the face.For facial application, spray onto thepalms or a cotton pad first, then gentlypat onto the face.

PURPOSE

Effectively blocks ultraviolet raysHelps protect skin from UVA& UVB damageLeaves skin feeling fresh andhydrated